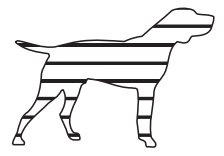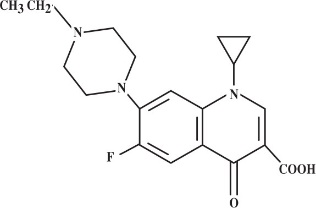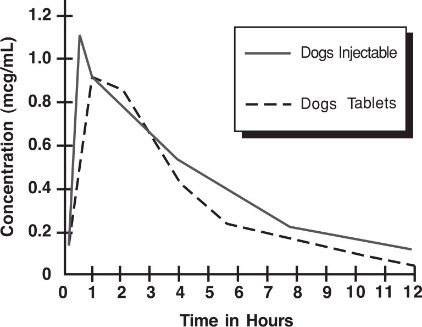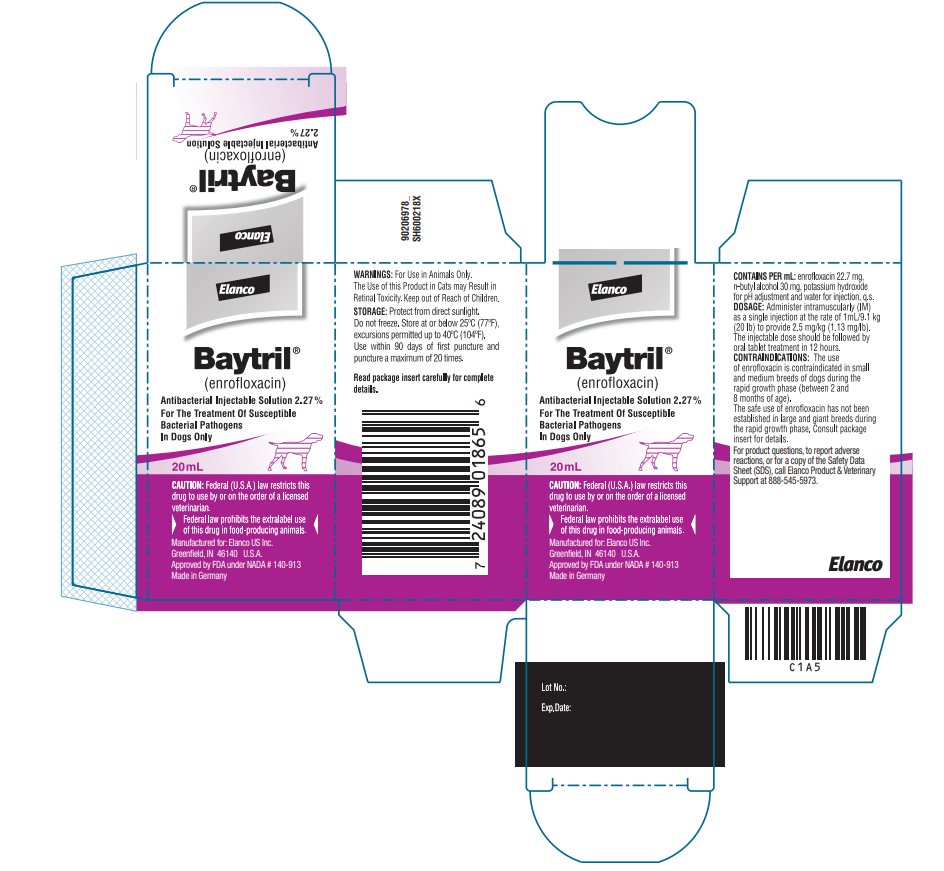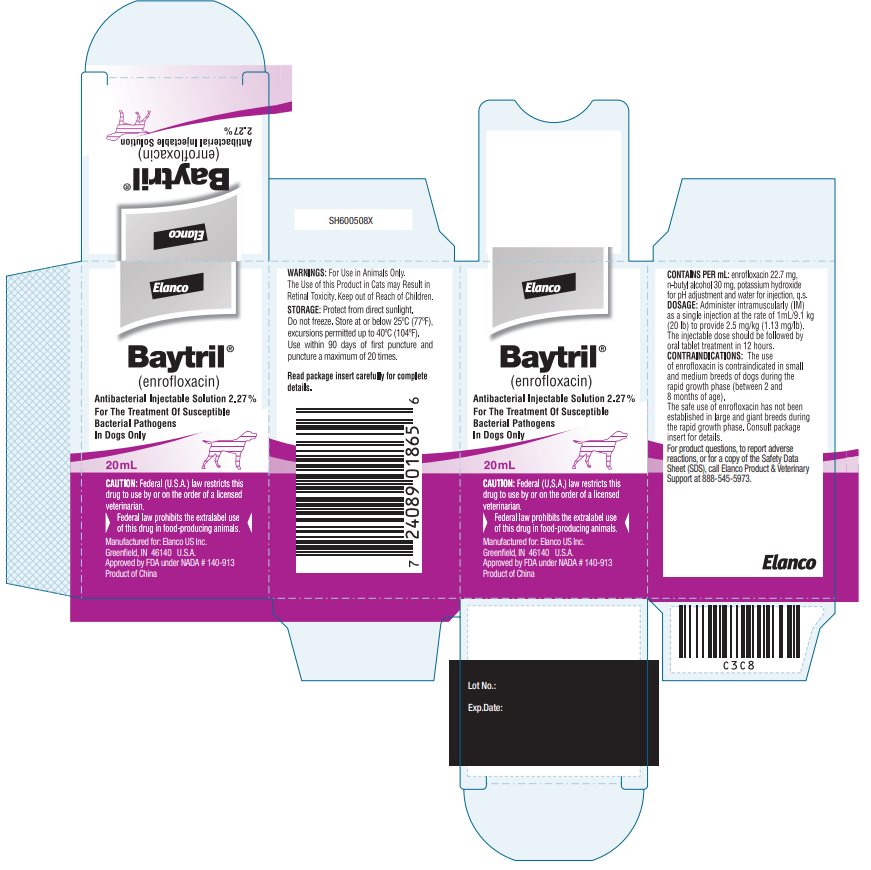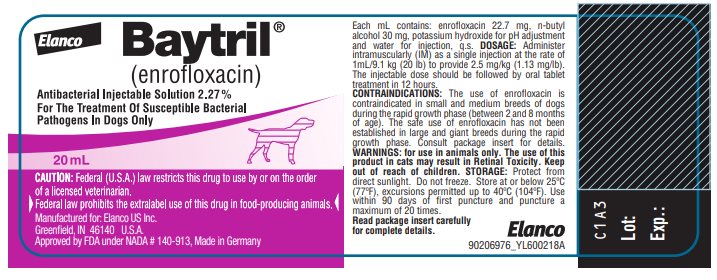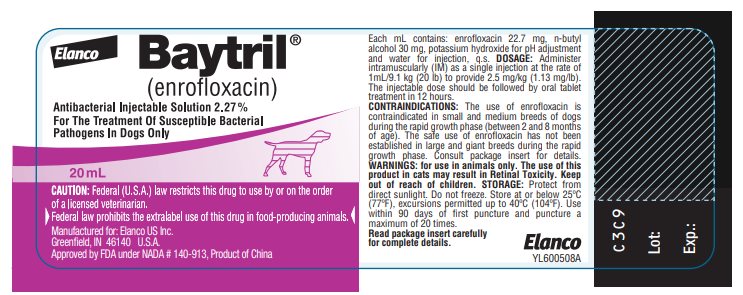 DRUG LABEL: Baytril
NDC: 58198-0020 | Form: INJECTION, SOLUTION
Manufacturer: Elanco US Inc.
Category: animal | Type: PRESCRIPTION ANIMAL DRUG LABEL
Date: 20250825

ACTIVE INGREDIENTS: ENROFLOXACIN 22.7 mg/1 mL; BUTYL ALCOHOL 30 mg/1 mL

Approved by FDA under NADA # 140-913

Elanco
Baytril®
(enrofloxacin)
Antibacterial Injectable Solution 2.27%
For Dogs Only

CAUTION:

Federal (U.S.A.) law restricts this drug to use by or on the order of a licensed veterinarian.

Federal law prohibits the extralabel use of this drug in food-producing animals.

DESCRIPTION:

Enrofloxacin is a synthetic chemotherapeutic agent from the class of the quinolone carboxylic acid derivatives. It has antibacterial activity against a broad spectrum of Gram negative and Gram positive bacteria (See Tables I and II). Each mL of injectable solution contains: enrofloxacin 22.7 mg, n-butyl alcohol 30 mg, potassium hydroxide for pH adjustment and water for injection, q.s.

CHEMICAL NOMENCLATURE AND STRUCTURAL FORMULA:

1-cyclopropyl-7-(4-ethyl-1-piperazinyl)-6-fluoro-1,4-dihydro-4-oxo-3-quinolinecarboxylic acid.

ACTIONS:

MICROBIOLOGY

Microbiology: Quinolone carboxylic acid derivatives are classified as DNA gyrase inhibitors. The mechanism of action of these compounds is very complex and not yet fully understood. The site of action is bacterial gyrase, a synthesis promoting enzyme. The effect on Escherichia coli is the inhibition of DNA synthesis through prevention of DNA supercoiling. Among other things, such compounds lead to the cessation of cell respiration and division. They may also interrupt bacterial membrane integrity.^1

Enrofloxacin is bactericidal, with activity against both Gram negative and Gram positive bacteria. The minimum inhibitory concentrations (MICs) were determined for a series of 37 isolates representing 9 genera of bacteria from natural infections in dogs, selected principally because of resistance to one or more of the following antibiotics: ampicillin, cephalothin, colistin, chloramphenicol, erythromycin, gentamicin, kanamycin, penicillin, streptomycin, tetracycline, triple sulfa and sulfa/trimethoprim. The MIC values for enrofloxacin against these isolates are presented in Table I. Most strains of these organisms were found to be susceptible to enrofloxacin in vitro but the clinical significance has not been determined for some of the isolates.

The susceptibility of organisms to enrofloxacin should be determined using enrofloxacin 5 mcg disks. Specimens for susceptibility testing should be collected prior to the initiation of enrofloxacin therapy.

TABLE I — MIC Values for Enrofloxacin Against Canine Pathogens (Diagnostic laboratory isolates, 1984)
Organisms | Isolates | MIC Range (mcg/mL)
Bacteroides spp. | 2 | 2
Bordetella bronchiseptica | 3 | 0.125-0.5
Brucella canis | 2 | 0.125-0.25
Clostridium perfringens | 1 | 0.5
Escherichia coli | 4 | <0.016-0.031
Klebsiella spp. | 10 | 0.031-0.5
Proteus mirabilis | 6 | 0.062-0.125
Pseudomonas aeruginosa | 4 | 0.5-8
Staphylococcus spp. | 5 | 0.125

The inhibitory activity on 120 isolates of seven canine urinary pathogens was also investigated and is listed in Table II.

TABLE II — MIC Values for Enrofloxacin Against Canine Urinary Pathogens (Diagnostic laboratory isolates, 1985)
Organisms | Isolates | MIC Range (mcg/ mL)
E coli | 30 | 0.06-2.0
P. mirabilis | 20 | 0.125-2.0
K. pneumoniae | 20 | 0.06-0.5
P. aeruginosa | 10 | 1.0-8.0
Enterobacter spp. | 10 | 0.06-1.0
Staph, (coag. +) | 20 | 0.125-0.5
Strep, (alpha hemol.) | 10 | 0.5-8.0

Distribution in the Body: Enrofloxacin penetrates into all canine tissues and body fluids. Concentrations of drug equal to or greater than the MIC for many pathogens (See Tables I, II and III) are reached in most tissues by two hours after dosing at 2.5 mg/kg and are maintained for 8-12 hours after dosing. Particularly high levels of enrofloxacin are found in urine. A summary of the body fluid/tissue drug levels at 2 to 12 hours after dosing at 2.5 mg/kg is given in Table III.

TABLE III — Body Fluid/Tissue distribution of Enrofloxacin in Dogs Single Oral Dose = 2.5 mg/kg (1.13 mg/lb) Post-treatment Enrofloxacin Levels Canine (n=2)
Body Fluids (mcg/mL) | 2 Hr. | 8 Hr.
Urine | 43.05 | 55.35
Eye Fluids | 0.53 | 0.66
Whole Blood | 1.01 | 0.36
Plasma | 0.67 | 0.33
Tissues (mcg/g) Hematopoietic System
Liver | 3.02 | 1.36
Spleen | 1.45 | 0.85
Bone Marrow | 2.10 | 1.22
Lymph Node | 1.32 | 0.91
Urogenital System
Kidney | 1.87 | 0.99
Bladder Wall | 1.36 | 0.98
Testes | 1.36 | 1.10
Prostate | 1.36 | 2.20
Uterine Wall | 1.59 | 0.29
Gastrointestinal and Cardiopulmonary Systems
Lung | 1.34 | 0.82
Heart | 1.88 | 0.78
Stomach | 3.24 | 2.16
Small Intestine | 2.10 | 1.11
Other
Fat | 0.52 | 0.40
Skin | 0.66 | 0.48
Muscle | 1.62 | 0.77
Brain | 0.25 | 0.24
Mammary Gland | 0.45 | 0.21
Feces | 1.65 | 9.97

PHARMACOKINETICS

Pharmacokinetics: In dogs, the absorption and elimination characteristics of the oral formulation are linear (plasma concentrations increase proportionally with dose) when enrofloxacin is administered at up to 11.5 mg/kg, twice daily.^2 Approximately 80% of the orally administered dose enters the systemic circulation unchanged. The eliminating organs, based on the drug's body clearance time, can readily remove the drug with no indication that the eliminating mechanisms are saturated. The primary route of excretion is via the urine. The absorption and elimination characteristics beyond this point are unknown. Saturable absorption and/or elimination processes may occur at greater doses. When saturation of the absorption process occurs, the plasma concentration of the active moiety will be less than predicted, based on the concept of dose proportionality.

Following an oral dose in dogs of 2.5 mg/kg (1.13 mg/lb), enrofloxacin reached 50% of its maximum serum concentration in 15 minutes and peak serum level was reached in one hour. The elimination half-life in dogs is approximately 2 ½ -3 hours at that dose.

A graph indicating the mean serum levels following a dose of 2.5 mg/kg (1.13 mg/lb) in dogs (oral and intramuscular) is shown in Figure 1.

Figure 1 - Serum Concentrations of Enrofloxacin Following a Single Oral or Intramuscular Dose at 2.5 mg/kg in Dogs.

Breakpoint: Based on pharmacokinetic studies of enrofloxacin in dogs after a single oral administration of 2.5 mg enrofloxacin/kg BW (i.e. half of the lowest-end single daily dose range) and the data listed in Tables I and II, the following breakpoints are recommended for canine isolates.

Zone Diameter (mm) | MIC (μg/mL) | Interpretation
≥ 21 | ≤ 0.5 | Susceptible(S)
18-20 | 1 | Intermediate (I)
≤ 17 | ≥ 2 | Resistant (R)

A report of “Susceptible” indicates that the pathogen is likely to be inhibited by generally achievable plasma levels. A report of "intermediate" is a technical buffer and isolates falling into this category should be retested. Alternatively the organism may be successfully treated if the infection is in a body site where drug is physiologically concentrated. A report of “resistant” indicates that the achievable drug concentrations are unlikely to be inhibitory and other therapy should be selected.

Standardized procedures require the use of laboratory control organisms for both standardized disk diffusion assays and standardized dilution assays. The 5 μg enrofloxacin disk should give the following zone diameters and enrofloxacin powder should provide the following MIC values for reference strains.

QC strain | MIC (μg/mL) | Zone Diameter (mm)
E. coli ATCC 25922 | 0.008 - 0.03 | 32 - 40
P. aeruginosa ATCC 27853 | 1 - 4 | 15- 19
S. aureus ATCC 25923 |  | 27 - 31
S. aureus ATCC 29213 | 0.03 - 0.12

INDICATIONS:

Baytril® (brand of enrofloxacin) Injectable Solution is indicated for the management of diseases in dogs associated with bacteria susceptible to enrofloxacin.

EFFICACY CONFIRMATION:

Clinical efficacy was established in dermal infections (wounds and abscesses) associated with susceptible strains of Escherichia coli, Klebsiella pneumoniae, Proteus mirabilis, and Staphylococcus intermedius, respiratory infections (pneumonia, tonsillitis, rhinitis) associated with susceptible strains of Escherichia coli and Staphylococcus aureus; and urinary cystitis associated with susceptible strains of Escherichia coli, Proteus mirabilis, and Staphylococcus aureus.

CONTRAINDICATIONS:

Enrofloxacin is contraindicated in dogs known to be hypersensitive to quinolones.

Based on the studies discussed under the section on Animal Safety Summary, the use of enrofloxacin is contraindicated in small and medium breeds of dogs during the rapid growth phase (between 2 and 8 months of age). The safe use of enrofloxacin has not been established in large and giant breeds during the rapid growth phase. Large breeds may be in this phase for up to one year of age and the giant breeds for up to 18 months. In clinical field trials utilizing a daily oral dose of 5.0 mg/kg, there were no reports of lameness or joint problems in any breed. However, controlled studies with histological examination of the articular cartilage have not been conducted in the large or giant breeds.

ADVERSE REACTIONS:

No drug-related side effects were reported in 122 clinical cases treated with Baytril (enrofloxacin) Injectable Solution followed by Baytril Tablets at 5.0 mg/kg per day.

For medical emergencies or to report adverse reactions, call 888-545-5973. For additional information about reporting adverse drug experiences for animal drugs, contact FDA at 1-888-FDA-VETS or http://www.fda.gov/reportanimalae.

ANIMAL SAFETY SUMMARY:

Adult dogs receiving enrofloxacin orally at a daily dosage rate 52 mg/kg for 13 weeks had only isolated incidences of vomition and inappetence. Adult dogs receiving the tablet formulation for 30 consecutive days at a daily treatment of 25 mg/kg did not exhibit significant clinical signs nor were there effects upon the clinical chemistry, hematological or histological parameters. Daily doses of 125 mg/kg for up to 11 days induced vomition, inappetence, depression, difficult locomotion and death while adult dogs receiving 50 mg/kg/day for 14 days had clinical signs of vomition and inappetence.

Adult dogs dosed intramuscularly for three treatments at 12.5 mg/kg followed by 57 oral treatments at 12.5 mg/kg, all at 12 hour intervals, did not exhibit either significant clinical signs or effects upon the clinical chemistry, hematological or histological parameters.

Oral treatment of 15 to 28 week old growing puppies with daily dosage rates of 25 mg/kg has induced abnormal carriage of the carpal joint and weakness in the hindquarters. Significant improvement of clinical signs is observed following drug withdrawal. Microscopic studies have identified lesions of the articular cartilage following 30 day treatments at either 5,15 or 25 mg/kg in this age group. Clinical signs of difficult ambulation or associated cartilage lesions have not been observed in 29 to 34 week old puppies following daily treatments of 25 mg/kg for 30 consecutive days nor in 2 week old puppies with the same treatment schedule.

Tests indicated no effect on circulating microfilariae or adult heart-worms (Dirofilaria immitis) when dogs were treated at a daily dosage rate of 15 mg/kg for 30 days. No effect on cholinesterase values was observed.

No adverse effects were observed on reproductive parameters when male dogs received 10 consecutive daily treatments of 15 mg/kg/day at 3 intervals (90, 45 and 14 days) prior to breeding or when female dogs received 10 consecutive daily treatments of 15 mg/kg/day at 4 intervals: between 30 and 0 days prior to breeding, early pregnancy (between 10th & 30th days), late pregnancy (between 40th & 60th days), and during lactation (the first 28 days).

DRUG INTERACTIONS:

Concomitant therapy with other drugs that are metabolized in the liver may reduce the clearance rates of the quinolone and the other drug.

Enrofloxacin has been administered to dogs at a daily dosage rate of 10 mg/kg concurrently with a wide variety of other health products including anthelmintics (praziquantel, febantel), insecticides (pyrethrins), heartworm preventatives (diethylcarbamazine) and other antibiotics (ampicillin, gentamicin sulfate, penicillin). No incompatibilities with other drugs are known at this time.

WARNINGS:

For use in animals only. The use of this product in cats may result in Retinal Toxicity. Keep out of reach of children.

Avoid contact with eyes. In case of contact, immediately flush eyes with copious amounts of water for 15 minutes. In case of dermal contact, wash skin with soap and water. Consult a physician if irritation persists following ocular or dermal exposure. Individuals with a history of hypersensitivity to quinolones should avoid this product. In humans, there is a risk of user photosensitization within a few hours after excessive exposure to quinolones. If excessive accidental exposure occurs, avoid direct sunlight.

For customer service or to obtain product information, including Safety Data Sheet, call 888-545-5973.

PRECAUTION:

Quinolone-class drugs should be used with caution in animals with known or suspected Central Nervous System (CNS) disorders. In such animals, quinolones have, in rare instances, been associated with CNS stimulation which may lead to convulsive seizures.

Quinolone-class drugs have been associated with cartilage erosions in weight-bearing joints and other forms of arthropathy in immature animals of various species.

The use of fluoroquinolones in cats has been reported to adversely affect the retina. Such products should be used with caution in cats.

DOSAGE AND ADMINISTRATION:

Baytril Injectable Solution may be used as the initial dose at 2.5 mg/kg. It should be administered intramuscularly (IM) as a single dose, followed by initiation of Baytril Tablet therapy.

Baytril Injectable Solution may be administered as follows:

Weight of Animal | Baytril Injectable Solution* 2.5 mg/kg
9.1 kg (20 lb) | 1.00 mL
27.2 kg (60 lb) | 3.00 mL
*The initial Baytril Injectable administration should be followed 12 hours later by initiation of Baytril Tablet therapy.

The lower limit of the dose range was based on efficacy studies in dogs where enrofloxacin was administered at 2.5 mg/kg twice daily. Target animal safety and toxicology studies were used to establish the upper limit of the dose range and treatment duration.

STORAGE:

Protect from direct sunlight. Do not freeze. Store at or below 25°C (77°F), excursions permitted up to 40°C (104°F).

Use within 90 days of first puncture and puncture a maximum of 20 times. Any product remaining after 20 punctures or more than 90 days after initial puncture should be discarded.

HOW SUPPLIED:

Baytril Injectable Solution
22.7 mg/mL Vial Size
20 mL

REFERENCES:

1. Dougherty, T.J. and Saukkonen, J.J. Membrane Permeability Changes Associated with DNA Gyrase Inhibitors in Escherichia coli. Antimicrob.Agents and Chemoth., V. 28, Aug. 1985:200-206.
2. Walker, R.D., et al. Pharmacokinetic Evaluation of Enrofloxacin Administered Orally to Healthy Dogs. Am.J. Res., V. 53, No. 12, Dec. 1992: 2315-2319.

90206975_PA600218X Revised: January 2022

Approved by FDA under NADA # 140-913

Baytril is sold by Elanco or its affiliates and is not a product of Bayer. The product name Baytril is owned by Bayer and used under license. Elanco and the diagonal bar logo are trademarks of Elanco or its affiliates.

© 2022 Elanco or its affiliates.

Elanco™
Manufactured for:
Elanco US Inc.
Greenfield, IN 46140 U.S.A.

Principal Display Panel - 20 mL Carton Label

Elanco

Baytril®
(enrofloxacin)

Antibacterial Injectable Solution 2.27%
For The Treatment Of Susceptible
Bacterial Pathogens
In Dogs Only

20 mL

CAUTION: Federal (U.S.A.) law restricts this
drug to use by or on the order of a licensed
veterinarian.

Federal law prohibits the extralabel use
of this drug in food-producing animals.

Manufactured for: Elanco US Inc.
Greenfield, IN 46140 U.S.A.
Approved by FDA under NADA # 140-913
Made in Germany

Elanco

Baytril®
(enrofloxacin)

Antibacterial Injectable Solution 2.27%
For The Treatment Of Susceptible
Bacterial Pathogens
In Dogs Only

20 mL

CAUTION: Federal (U.S.A.) law restricts this
drug to use by or on the order of a licensed
veterinarian.

Federal law prohibits the extralabel use
of this drug in food-producing animals.

Manufactured for: Elanco US Inc.
Greenfield, IN 46140 U.S.A.
Approved by FDA under NADA # 140-913
Product of China

Principal Display Panel - Bottle Label

Elanco

Baytril®
(enrofloxacin)

Antibacterial Injectable Solution 2.27%
For The Treatment Of Susceptible Bacterial
Pathogens In Dogs Only

20 mL

CAUTION: Federal (U.S.A.) law restricts this drug to use by or on the order
of a licensed veterinarian.

Federal law prohibits the extralabel use of this drug in food-producing animals.

Manufactured for: Elanco US Inc.
Greenfield, IN 46140 U.S.A.
Approved by FDA under NADA # 140-913, Made in Germany

Elanco

Baytril®
(enrofloxacin)

Antibacterial Injectable Solution 2.27%
For The Treatment Of Susceptible Bacterial
Pathogens In Dogs Only

20 mL

CAUTION: Federal (U.S.A.) law restricts this drug to use by or on the order
of a licensed veterinarian.

Federal law prohibits the extralabel use of this drug in food-producing animals.

Manufactured for: Elanco US Inc.
Greenfield, IN 46140 U.S.A.
Approved by FDA under NADA # 140-913, Product of China